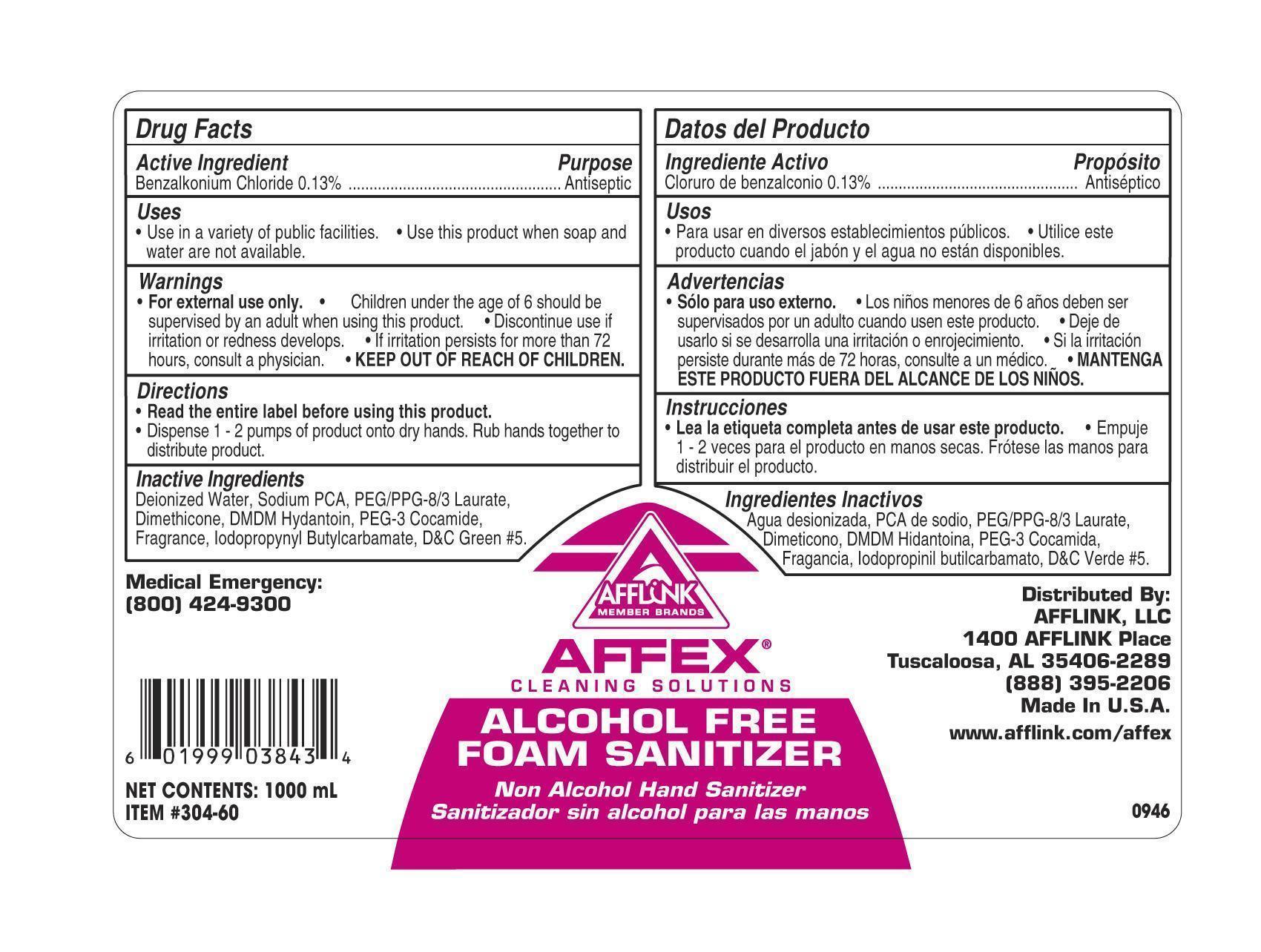 DRUG LABEL: Alcohol Free Foam Sanitizer
NDC: 54057-304 | Form: SOAP
Manufacturer: Afflink, Inc.
Category: otc | Type: HUMAN OTC DRUG LABEL
Date: 20121213

ACTIVE INGREDIENTS: BENZALKONIUM CHLORIDE 1.3 mg/1 mL
INACTIVE INGREDIENTS: WATER; SODIUM PYRROLIDONE CARBOXYLATE; POLYETHYLENE GLYCOL 400; DIMETHICONE; DMDM HYDANTOIN; PEG-6 COCAMIDE; IODOPROPYNYL BUTYLCARBAMATE; D&C GREEN NO. 5

Alcohol Free Foam Sanitizer

Alcohol Free Foam Sanitizer

Active Ingredient

Benzalkonium Chloride 0.13%

Alcohol Free Foam Sanitizer

Uses

- Use in a variety of public facilities.
- Use this product when soap and water are not available.

Alcohol Free Foam Sanitizer

Warnings

- For external use only.
- Avoid contact with eyes.
- Children under the age of 6 should be supervised by an adult when using this product.
- Discontinue use is irritation or redness develops.
- If irritation persists for more than 72 hours, consult a physician.
- KEEP OUT OF REACH OF CHILDREN.

Alcohol Free Foam Sanitizer

Directions

- Read the entire label before using this product.
- Dispense 1-2 pumps of product onto dry hands. Rub hands together to distribute product

Alcohol Free Foam Sanitizer

Inactive Ingredients

Deionized Water, Sodium PCA, PEG/PPG-8/3 Laurate, Dimethicone, DMDM Hydantoin, PEG-3 Cocamide, Fragrance, Iodoproynyl Btylcarbamate, D&C Green #5.

Alcohol Free Foam Sanitizer

Purpose

Antiseptic

Alcohol Free Foam Sanitizer

KEEP OUT OF REACH OF CHILDREN

Alcohol Free Foam Sanitizer

AFFEX Cleaning Solutions

Alcohol Free Foam Sanitizer

Non Alcohol hand Sanitizer

Mediucal Emergency:

(800)424-9300

NET CONTENTS: 1000 mL

ITEM #304-60